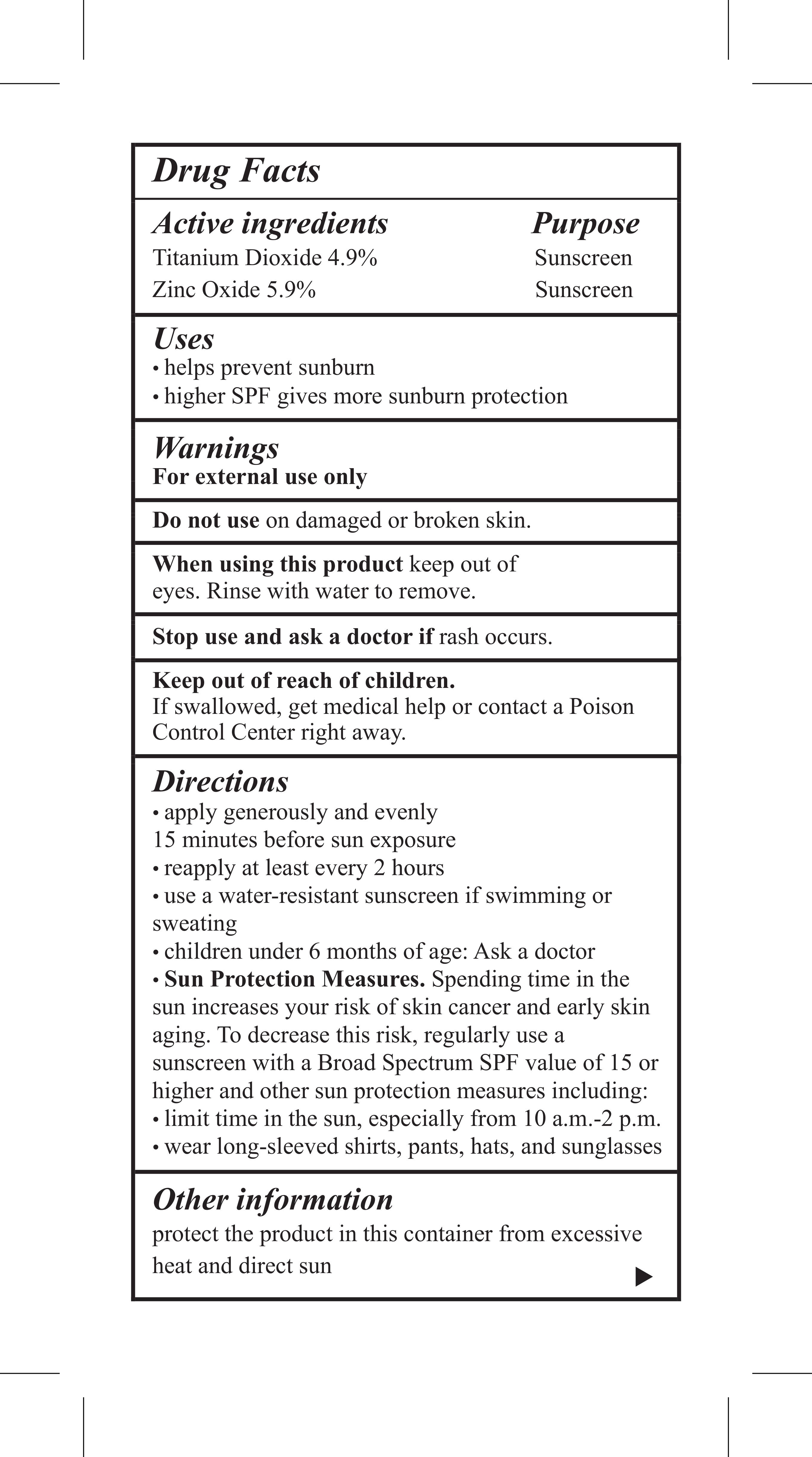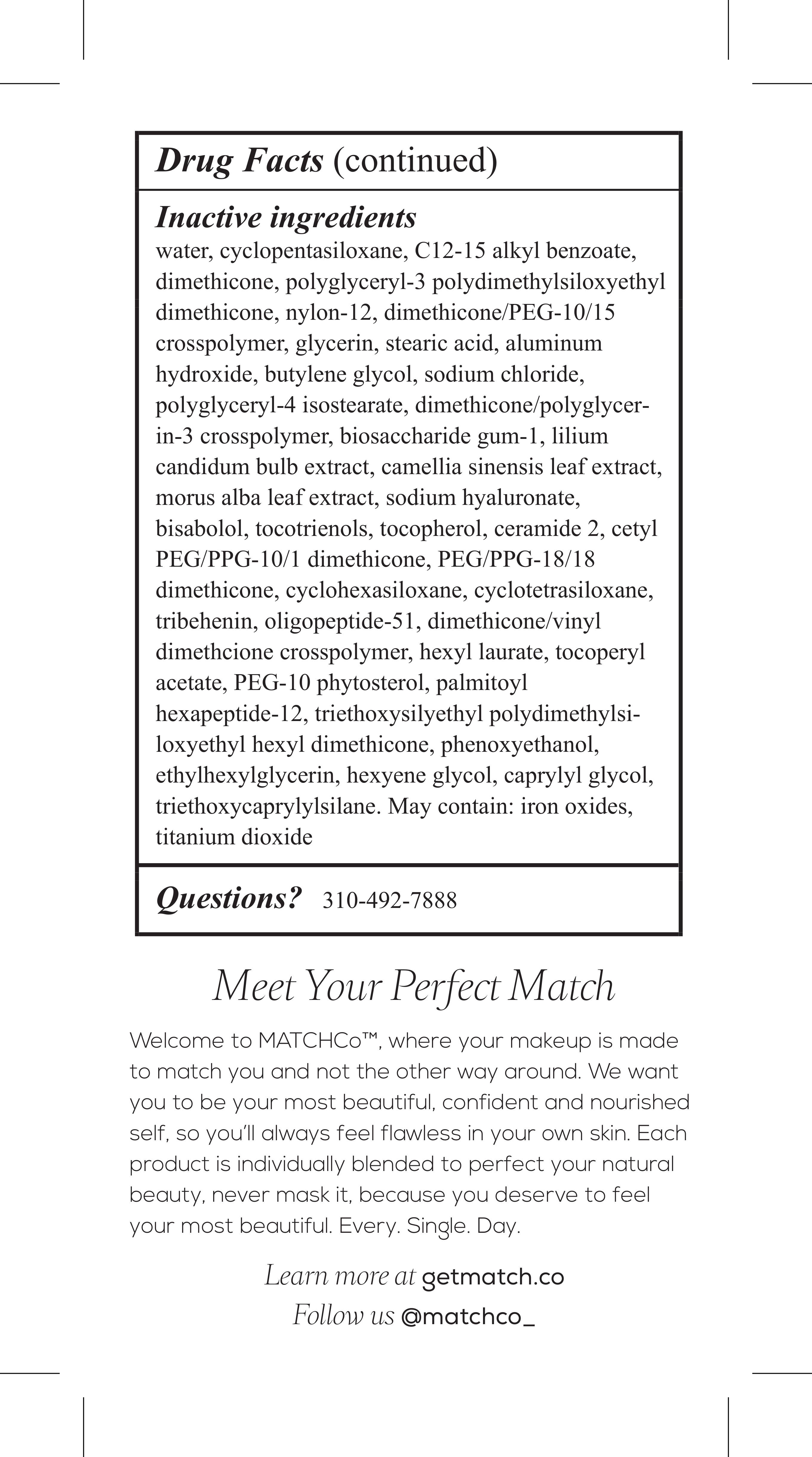 DRUG LABEL: zinc oxide, titanium dioxide
NDC: 70798-415 | Form: CREAM
Manufacturer: MATCHCo Inc.
Category: otc | Type: HUMAN OTC DRUG LABEL
Date: 20160512

ACTIVE INGREDIENTS: TITANIUM DIOXIDE 4.9 mg/1 g; ZINC OXIDE 5.9 mg/1 g
INACTIVE INGREDIENTS: WATER; POLYGLYCERYL-3 POLYDIMETHYLSILOXYETHYL DIMETHICONE (4000 MPA.S); FERROSOFERRIC OXIDE; STEARIC ACID; ALUMINUM HYDROXIDE; BUTYLENE GLYCOL; SODIUM CHLORIDE; POLYGLYCERYL-4 ISOSTEARATE; BIOSACCHARIDE GUM-1; MORUS ALBA LEAF; HYALURONATE SODIUM; TOCOPHEROL; CERAMIDE 2; TRIBEHENIN; LEVOMENOL; CETYL PEG/PPG-10/1 DIMETHICONE (HLB 2); DIMETHICONE/VINYL DIMETHICONE CROSSPOLYMER (SOFT PARTICLE); PALMITOYL TRIPEPTIDE-1; CYCLOMETHICONE 5; ALKYL (C12-15) BENZOATE; DIMETHICONE; NYLON-12; GLYCERIN; LILIUM CANDIDUM BULB; GREEN TEA LEAF; TOCOTRIENOLS; PEG/PPG-18/18 DIMETHICONE; CYCLOMETHICONE 6; CYCLOMETHICONE 4; HEXYL LAURATE; ALPHA-TOCOPHEROL ACETATE; HEXYLENE GLYCOL; PHENOXYETHANOL; ETHYLHEXYLGLYCERIN; CAPRYLYL GLYCOL; FERRIC OXIDE RED; FERRIC OXIDE YELLOW; TRIETHOXYCAPRYLYLSILANE

STATEMENT OF IDENTITY SECTION

Drug Facts

Active ingredients Purpose

Titanium Dioxide 4.0% Sunscreen

Zinc Oxide 5.9% Sunscreen

INDICATIONS AND USAGE SECTION

Uses

- helps prevent sunburn
- higher SPF gives more sunburn protection

Warnings

For external use only

Do not use on damaged or broken skin.

When using this product keep out of eyes. Rinse with water to remove.

Stop use and ask a doctor if rash occurs.

Keep out of reach of children.

If swallowed, get medical help or contact a Poison Control Center right away.

WARNINGS SECTION

Warnings

For external use only

Do not use on damaged or broken skin.

When using this product keep out of eyes. Rinse with water to remove.

Stop use and ask a doctor if rash occurs.

Keep out of reach of children.

If swallowed, get medical help or contact a Poison Control Center right away.

OTHER SAFETY INFORMATION

Other information

protect the product in this container from excessive heat and direct sun

OTC - ACTIVE INGREDIENT SECTION

Active ingredients Purpose

Titanium Dioxide 4.9% Sunscreen

Zinc Oxide 5.9% Sunscreen

OTC - STOP USE SECTION

Stop use and ask doctor if rash occurs.

Principal Display Panel

Dist. By.

MATCHCo, Inc

Santa Monica, CA 90401